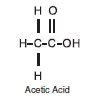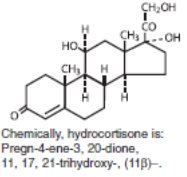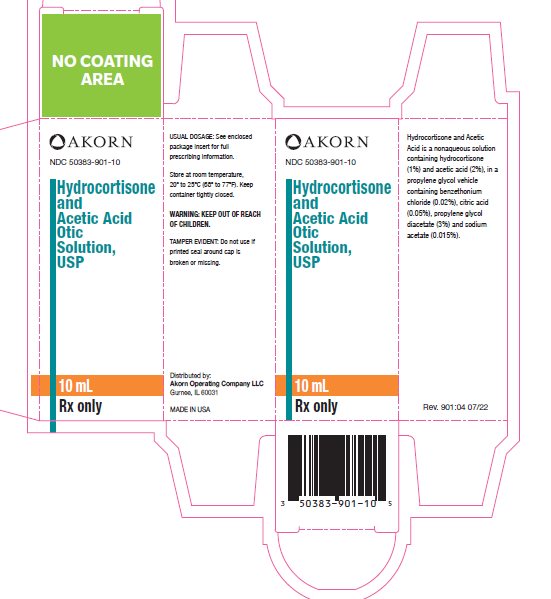 DRUG LABEL: hydrocortisone and acetic acid
NDC: 50383-901 | Form: SOLUTION
Manufacturer: Akorn Operating Company LLC
Category: prescription | Type: HUMAN PRESCRIPTION DRUG LABEL
Date: 20221013

ACTIVE INGREDIENTS: ACETIC ACID 20.75 mg/1 mL; HYDROCORTISONE 10.375 mg/1 mL
INACTIVE INGREDIENTS: ANHYDROUS CITRIC ACID; BENZETHONIUM CHLORIDE; PROPYLENE GLYCOL; PROPYLENE GLYCOL DIACETATE; SODIUM ACETATE

Hydrocortisone and Acetic Acid Otic Solution, USP

DESCRIPTION

Hydrocortisone and Acetic Acid Otic Solution, USP is a solution containing hydrocortisone (1%) and acetic acid (2%), in a propylene glycol vehicle containing benzethonium chloride (0.02%), citric acid (0.05%), propylene glycol diacetate (3%) and sodium acetate (0.015%). The empirical formulas for acetic acid and hydrocortisone are CH3COOH, and C21H30O5, with a molecular weight of 60.05 and 362.46, respectively. The structural formulas are:

Hydrocortisone and Acetic Acid is available as a nonaqueous otic solution buffered at pH 3 for use in the external ear canal.

CLINICAL PHARMACOLOGY

Acetic acid is antibacterial and antifungal; hydrocortisone is antiinflammatory, antiallergic and antipruritic; propylene glycol is hydrophilic and provides a low surface tension; benzethonium chloride is a surface active agent that promotes contact of the solution with tissues.

INDICATIONS AND USAGE

For the treatment of superficial infections of the external auditory canal caused by organisms susceptible to the action of the antimicrobial, complicated by inflammation.

CONTRAINDICATIONS

Hypersensitivity to Hydrocortisone and Acetic Acid or any of the ingredients; herpes simplex, vaccinia and varicella. Perforated tympanic membrane is considered a contraindication to the use of any medication in the external ear canal.

WARNINGS

Discontinue promptly if sensitization or irritation occurs.

PRECAUTIONS

Transient stinging or burning may be noted occasionally when the solution is first instilled into the acutely inflamed ear.

Pediatric Use

Safety and effectiveness in pediatric patients below the age of 3 years have not been established.

ADVERSE REACTIONS

Stinging or burning may be noted occasionally; local irritation has occurred very rarely.

DOSAGE AND ADMINISTRATION

Carefully remove all cerumen and debris to allow Hydrocortisone and Acetic Acid to contact infected surfaces directly. To promote continuous contact, insert a wick of cotton saturated with Hydrocortisone and Acetic Acid into the ear canal; the wick may also be saturated after insertion. Instruct the patient to keep the wick in for at least 24 hours and to keep it moist by adding 3 to 5 drops of Hydrocortisone and Acetic Acid every 4 to 6 hours. The wick may be removed after 24 hours but the patient should continue to instill 5 drops of Hydrocortisone and Acetic Acid 3 or 4 times daily thereafter, for as long as indicated. In pediatric patients, 3 to 4 drops may be sufficient due to the smaller capacity of the ear canal.

HOW SUPPLIED

Hydrocortisone and Acetic Acid Otic Solution, USP, containing hydrocortisone (1%) and acetic acid (2%), is available in 10 mL, measured-drop, safety-tip plastic bottles (NDC 50383-901-10).

STORAGE

Store at room temperature, 20° to 25°C (68° to 77°F).

Keep container tightly closed.

Rx only

Distributed by:

Akorn Operating Company LLC

Gurnee, IL 60031

Rev. 901:04 07/22

PACKAGE/LABEL PRINCIPAL DISPLAY PANEL

AKORN

NDC 50383-901-10

Hydrocortisone and Acetic Acid Otic Solution, USP

10 mL

Rx only